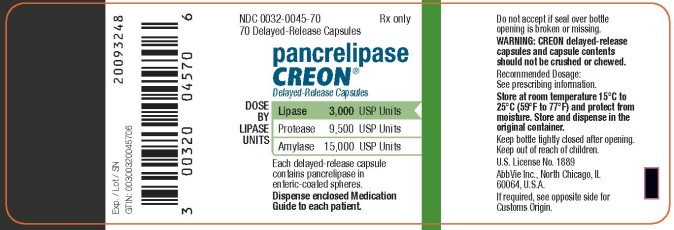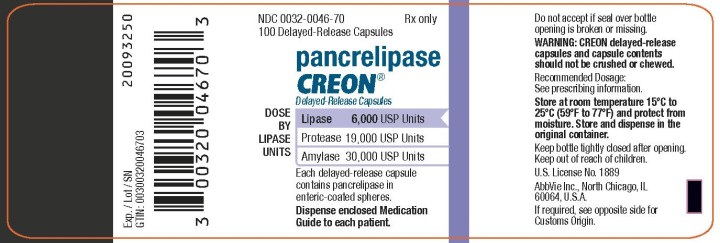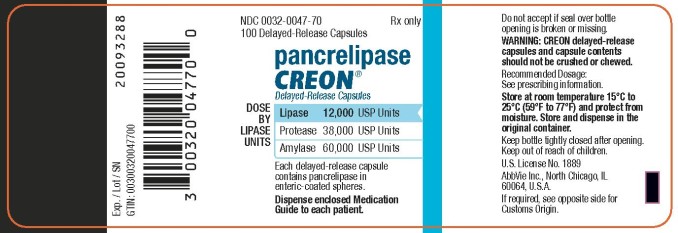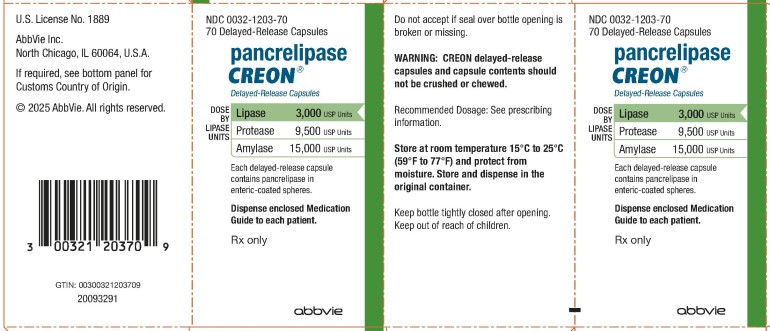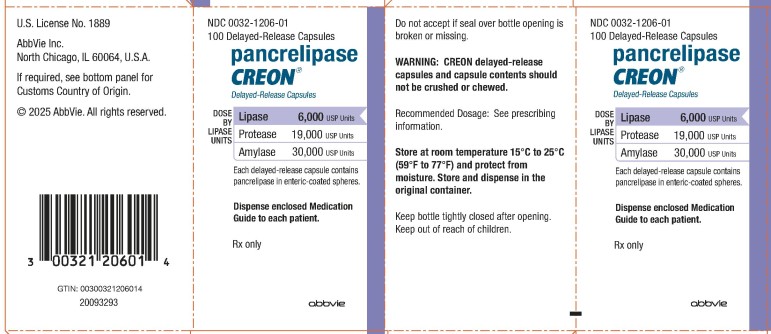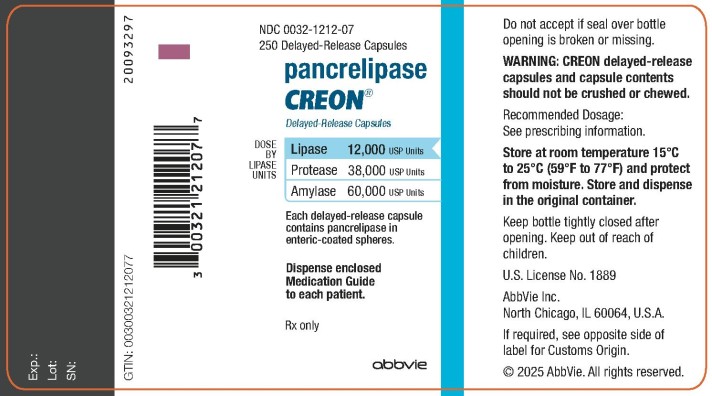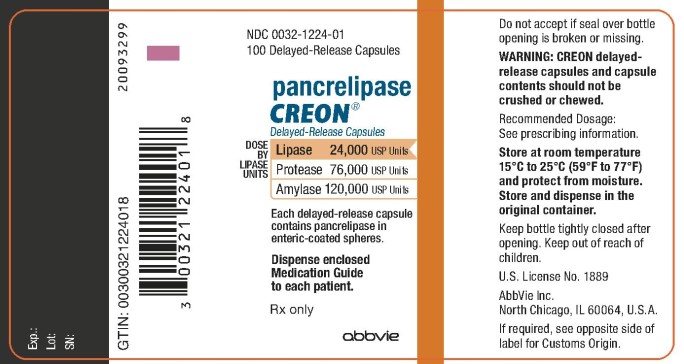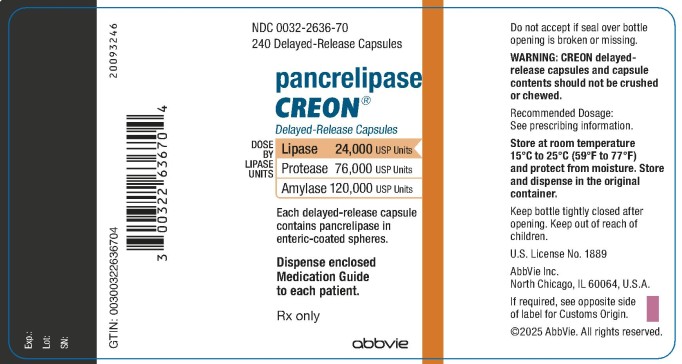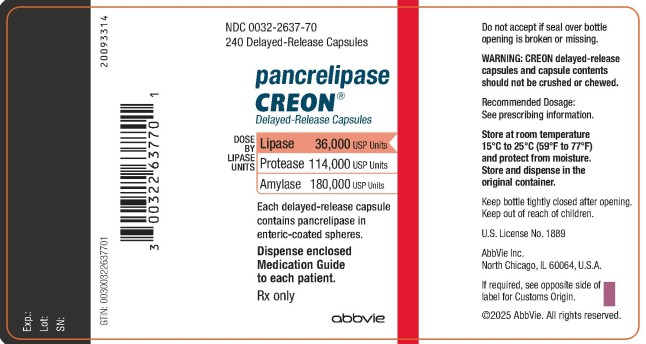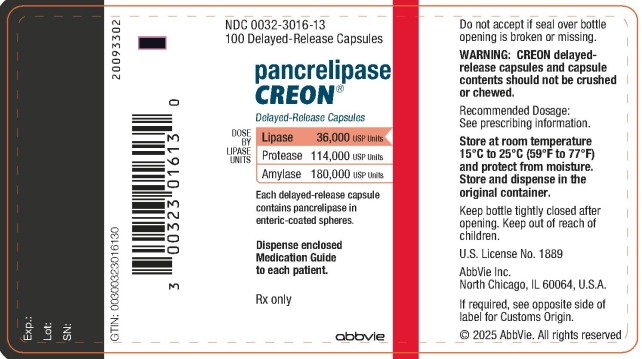 DRUG LABEL: Creon
NDC: 0032-1203 | Form: CAPSULE, DELAYED RELEASE
Manufacturer: AbbVie Inc.
Category: prescription | Type: HUMAN PRESCRIPTION DRUG LABEL
Date: 20240228

ACTIVE INGREDIENTS: PANCRELIPASE AMYLASE 15000 [USP'U]/1 1; PANCRELIPASE LIPASE 3000 [USP'U]/1 1; PANCRELIPASE PROTEASE 9500 [USP'U]/1 1
INACTIVE INGREDIENTS: CETYL ALCOHOL; DIMETHICONE; HYPROMELLOSE PHTHALATE (31% PHTHALATE, 40 CST); POLYETHYLENE GLYCOL, UNSPECIFIED; TRIETHYL CITRATE; HYPROMELLOSE, UNSPECIFIED; TITANIUM DIOXIDE; CARRAGEENAN; POTASSIUM CHLORIDE

HIGHLIGHTS OF PRESCRIBING INFORMATION

These highlights do not include all the information needed to use CREON safely and effectively. See full prescribing information for CREON.
CREON (pancrelipase) delayed-release capsules, for oral use
Initial U.S. Approval: 2009

1 INDICATIONS AND USAGE

CREON is indicated for the treatment of exocrine pancreatic insufficiency in adult and pediatric patients.

2 DOSAGE AND ADMINISTRATION

Important Dosing Information (2.1)

- CREON is a mixture of enzymes including lipases, proteases, and amylases, and dosing is based on lipase units. Dosing scheme based on actual body weight or fat ingestion.
- Individualize the dosage based on clinical symptoms, the degree of steatorrhea present, and the fat content of the diet.
- Do not exceed 2,500 lipase units/kg/meal, 10,000 lipase units/kg/day, or 4,000 lipase units/g fat ingested/day in adult and pediatric patients greater than 12 months of age without further investigation. (5.1)
- The total daily dosage in adult and pediatric patients greater than 12 months of age should reflect approximately three meals plus two or three snacks per day. With each snack, administer approximately half the prescribed dose for a meal.
- Do not substitute other pancreatic enzyme products for CREON. When switching from another pancreatic enzyme product to CREON, monitor patients for clinical symptoms of exocrine pancreatic insufficiency and titrate the dosage as needed.

Recommended Dosage (2.2)

Adult and Pediatric Patients Greater than 12 Months: The recommended initial starting dosage is:

- 500 lipase units/kg/meal for adult and pediatric patients 4 years and older.
- 500 to 1,000 lipase units/kg/meal for adult patients with chronic pancreatitis or pancreatectomy.
- 1,000 lipase units/kg/meal for pediatric patients greater than 12 months to less than 4 years.
- Titrate the dosage to either 2,500 lipase units/kg/meal, 10,000 lipase units/kg/day, or 4,000 lipase units/g fat ingested/day. Higher dosages may be administered if documented effective by fecal fat measures or improvement of malabsorption.

Pediatric Patients Birth to 12 Months: The recommended dosage is 3,000 lipase units (one capsule) per 120 mL of formula or per breastfeeding.

Preparation and Administration Instructions (2.3)

- Swallow capsules whole. For patients unable to swallow intact capsule(s), the capsule contents may be sprinkled on soft acidic food (e.g., applesauce, bananas, plain Greek yogurt).
- Do not crush or chew CREON capsules or capsule contents.
- Consume sufficient liquids to ensure complete swallowing of CREON. (5.2)
- See the full prescribing information for additional information on administering to pediatric patients birth to 12 months.

3 DOSAGE FORMS AND STRENGTHS

Delayed-Release Capsules (3):

- 3,000 USP units of lipase; 9,500 USP units of protease; and 15,000 USP units of amylase
- 6,000 USP units of lipase; 19,000 USP units of protease; and 30,000 USP units of amylase
- 12,000 USP units of lipase; 38,000 USP units of protease; and 60,000 USP units of amylase
- 24,000 USP units of lipase; 76,000 USP units of protease; and 120,000 USP units of amylase
- 36,000 USP units of lipase; 114,000 USP units of protease; and 180,000 USP units of amylase

4 CONTRAINDICATIONS

None (4)

5 WARNINGS AND PRECAUTIONS

- Fibrosing Colonopathy: Associated with high doses, usually over prolonged use and in pediatric patients with cystic fibrosis. Colonic stricture reported in pediatric patients less than 12 years of age with dosages exceeding 6,000 lipase units/kg/meal. Monitor during treatment for progression of preexisting disease. Do not exceed the recommended dosage, unless clinically indicated. (2.1, 5.1)
- Irritation of the Oral Mucosa: May occur due to loss of protective enteric coating on the capsule contents. (2.3, 5.2)
- Hyperuricemia: Reported with high dosages; consider monitoring blood uric acid levels in patients with gout, renal impairment, or hyperuricemia. (5.3)
- Risk of Viral Transmission: The presence of porcine viruses that might infect humans cannot be definitely excluded. (5.4)
- Hypersensitivity Reactions: Monitor patients with known reactions to proteins of porcine origin. If symptoms occur, initiate appropriate medical management; consider the risks and benefits of continued treatment. (5.5)

6 ADVERSE REACTIONS

Most Common Adverse Reactions (6.1)

Cystic fibrosis adult and pediatric patients:

- 7 years and older (≥4%): vomiting, dizziness, cough.
- 4 months to 6 years (6%): vomiting, irritability, decreased appetite.

Chronic pancreatitis or pancreatectomy patients:

- Adults (≥ 4%): hyperglycemia, hypoglycemia, abdominal pain, abnormal feces, flatulence, frequent bowel movements, nasopharyngitis.

To report SUSPECTED ADVERSE REACTIONS, contact AbbVie Inc. at 1-800-633-9110 or FDA at 1-800-FDA-1088 or www.fda.gov/medwatch.

FULL PRESCRIBING INFORMATION

1 INDICATIONS AND USAGE

CREON® is indicated for the treatment of exocrine pancreatic insufficiency in adult and pediatric patients.

2 DOSAGE AND ADMINISTRATION

2.1 Important Dosing Information

CREON is a mixture of enzymes including lipases, proteases, and amylases. CREON dosing is based on lipase units.

- Use either an actual body weight or fat ingestion-based dosing scheme.
- Start at the lowest recommended dosage and individualize the dosage based on clinical symptoms, the degree of steatorrhea present, and the fat content of the diet. Changes in dosage may require an adjustment period of several days.
- Do not exceed 2,500 lipase units/kg/meal, 10,000 lipase units/kg/day, or 4,000 lipase units/g fat ingested/day in adult and pediatric patients greater than 12 months of age without further investigation [see Warnings and Precautions (5.1)].
- The total daily dosage in adult and pediatric patients greater than 12 months of age should reflect approximately three meals plus two or three snacks per day. With each snack, administer approximately half the prescribed CREON dose for a meal.
- Do not substitute other pancreatic enzyme products for CREON. When switching from another pancreatic enzyme product to CREON, monitor patients for clinical symptoms of exocrine pancreatic insufficiency and titrate the dosage as needed.

2.2 Recommended Dosage

Adult and Pediatric Patients Greater than 12 Months of Age

The recommended oral initial starting dosage is:

- 500 lipase units/kg/meal for adult and pediatric patients 4 years of age and older.
- 500 to 1,000 lipase units/kg/meal for adult patients with chronic pancreatitis or pancreatectomy.
- 1,000 lipase units/kg/meal for pediatric patients greater than 12 months to less than 4 years of age.

If signs and symptoms of malabsorption persist, increase the dosage. Titrate to either 2,500 lipase units/kg/meal, 10,000 lipase units/kg/day, or 4,000 lipase units/gram of fat ingested/day. Higher dosages may be administered if they are documented to be effective by fecal fat measures or an improvement in signs or symptoms of malabsorption including measures of nutritional status.

Pediatric Patients Birth to 12 Months of Age

The recommended oral dosage is 3,000 lipase units per 120 mL of formula or per breast-feeding.

2.3 Preparation and Administration Instructions

Instruct adult and pediatric patients greater than 12 months of age, or their caregivers, of the following:

- Take CREON during meals and snacks. If a dose is missed, take the next dose with the next meal or snack.
- Swallow capsules whole.
- For patients who are unable to swallow intact capsules, carefully open the capsules and sprinkle the entire contents on a small amount of acidic soft food with a pH of 4.5 or less (e.g., applesauce, bananas, plain Greek yogurt). Consume the entire mixture immediately.
- Do not crush or chew CREON capsules or capsule contents.
- Consume sufficient liquids (water or juice) to ensure complete swallowing of CREON [see Warnings and Precautions (5.2)].

Instruct caregivers of pediatric patients birth to 12 months of age of the following:

- Immediately prior to each breast-feeding session or each administration of 120 mL of formula, carefully open one CREON capsule (containing 3,000 USP units of lipase) and administer the entire contents using one of the following two methods:
  - Sprinkle on a small amount of acidic soft food with a pH of 4.5 or less (e.g., applesauce, bananas, plain Greek yogurt) being careful not to crush the capsule contents. The entire mixture should be given to the infant immediately.
  - Sprinkle the capsule contents directly into the infant’s mouth.
- Immediately administer additional breast milk or formula after CREON to ensure complete swallowing of the capsule contents.
- Do not mix CREON capsule contents directly into a bottle of breast milk or formula.
- Do not crush CREON capsule contents, and visually inspect the infant’s mouth to ensure that no drug is retained in the mouth [see Warnings and Precautions (5.2)].
- If a dose is missed, administer the next dose with the next feeding.

3 DOSAGE FORMS AND STRENGTHS

Delayed-release capsules are available in the following strengths:

- 3,000 USP units of lipase; 9,500 USP units of protease; and 15,000 USP units of amylase in a two-piece capsule with a white opaque cap imprinted with “CREON 1203” and a white opaque body.
- 6,000 USP units of lipase; 19,000 USP units of protease; and 30,000 USP units of amylase in a two-piece capsule with an orange opaque cap imprinted with “CREON 1206” and a blue opaque body.
- 12,000 USP units of lipase; 38,000 USP units of protease; and 60,000 USP units of amylase in a two-piece capsule with a brown opaque cap imprinted with “CREON 1212” and a colorless transparent body.
- 24,000 USP units of lipase; 76,000 USP units of protease; and 120,000 USP units of amylase in a two-piece capsule with an orange opaque cap imprinted with “CREON 1224” and a colorless transparent body.
- 36,000 USP units of lipase; 114,000 USP units of protease; and 180,000 USP units of amylase in a two-piece capsule with a blue opaque cap imprinted with “CREON 1236” and a colorless transparent body.

4 CONTRAINDICATIONS

None.

5 WARNINGS AND PRECAUTIONS

5.1 Fibrosing Colonopathy

Fibrosing colonopathy has been reported following treatment with pancreatic enzyme products. Fibrosing colonopathy is a rare, serious adverse reaction initially described in association with use of high-dose pancreatic enzyme products, usually over a prolonged period of time and most commonly reported in pediatric patients with cystic fibrosis. Pancreatic enzyme products exceeding 6,000 lipase units/kg/meal have been associated with colonic stricture, a complication of fibrosing colonopathy, in pediatric patients less than 12 years of age. The underlying mechanism of fibrosing colonopathy remains unknown.

If there is history of fibrosing colonopathy, monitor patients during treatment with CREON because some patients may be at risk of progressing to colonic stricture formation. It is uncertain whether regression of fibrosing colonopathy occurs. Do not exceed the recommended dosage of either 2,500 lipase units/kg/meal, 10,000 lipase units/kg/day, or 4,000 lipase units/g fat ingested/day in adult and pediatric patients greater than 12 months of age without further investigation. Higher dosages may be administered if they are documented to be effective by fecal fat measures or an improvement in signs or symptoms of malabsorption including measures of nutritional status. Patients receiving dosages higher than 6,000 lipase units/kg/meal should be frequently monitored for symptoms of fibrosing colonopathy and the dosage decreased or titrated downward to a lower range if clinically appropriate [see Dosage and Administration (2.1)].

5.2 Irritation of the Oral Mucosa

Crushing or chewing CREON capsules or mixing the capsule contents in foods having a pH greater than 4.5 can disrupt the protective enteric coating on the capsule contents and result in early release of enzymes, irritation of the oral mucosa, and/or loss of enzyme activity.

Instruct the patient or caregiver of the following:

- Swallow capsules whole. For patients who cannot swallow the capsules whole, the capsules can be opened, and the contents sprinkled in a small amount of acidic soft food with a pH of 4.5 or less (e.g., applesauce, bananas, plain Greek yogurt).
- Do not crush or chew CREON capsules or capsule contents.
- Consume sufficient liquids (juice, water, breast milk, or formula) immediately following administration of CREON to ensure complete swallowing.
- Visually inspect the mouth of pediatric patients less than 12 months of age and of patients who are unable to swallow intact capsules to ensure no drug is retained in the mouth and irritation of the oral mucosa has not occurred [see Dosage and Administration (2.3)].

5.3 Hyperuricemia

Pancreatic enzyme products contain purines that may increase blood uric acid levels. High dosages have been associated with hyperuricosuria and hyperuricemia [see Overdosage (10)]. Consider monitoring blood uric acid levels in patients with gout, renal impairment, or hyperuricemia during treatment with CREON.

5.4 Risk of Viral Transmission

CREON is sourced from pancreatic tissue from swine used for food consumption. Although the risk that CREON will transmit an infectious agent to humans has been reduced by testing for certain viruses during manufacturing and by inactivating certain viruses during manufacturing, there is a theoretical risk for transmission of viral disease, including diseases caused by novel or unidentified viruses. Thus, the presence of porcine viruses that might infect humans cannot be definitely excluded. However, no cases of transmission of an infectious illness associated with the use of porcine pancreatic extracts have been reported.

5.5 Hypersensitivity Reactions

Severe hypersensitivity reactions including anaphylaxis, asthma, hives, and pruritus have been reported with pancreatic enzyme products [see Adverse Reactions (6.2)]. If symptoms occur, initiate appropriate medical management.

Monitor patients with a known hypersensitivity reaction to proteins of porcine origin for hypersensitivity reactions during treatment with CREON. The risks and benefits of continued CREON treatment in patients with severe hypersensitivity reactions should be taken into consideration with the overall clinical needs of the patient.

6 ADVERSE REACTIONS

The following serious or otherwise important adverse reactions are described elsewhere in the labeling:

- Fibrosing Colonopathy [see Warnings and Precautions (5.1)]
- Irritation of the Oral Mucosa [see Warnings and Precautions (5.2)]
- Hyperuricemia [see Warnings and Precautions (5.3)]
- Risk of Viral Transmission [see Warnings and Precautions (5.4)]
- Hypersensitivity Reactions [see Warnings and Precautions (5.5)]

6.1 Clinical Trials Experience

Because clinical trials are conducted under widely varying conditions, adverse reaction rates observed in the clinical trials of a drug cannot be directly compared to the rates in the clinical trials of another drug and may not reflect the rates observed in practice.

The data described below reflect exposure to CREON in 92 patients: 67 patients aged 4 months to 43 years with exocrine pancreatic insufficiency due to cystic fibrosis (Studies 1, 2, and 3) and 25 adults with exocrine pancreatic insufficiency due to chronic pancreatitis or pancreatectomy (Study 4) [see Use in Specific Populations (8.4) and Clinical Studies (14.1, 14.2)].

Exocrine Pancreatic Insufficiency Due to Cystic Fibrosis in Adult and Pediatric Patients

Adult and Pediatric Patients 7 Years of Age and Older

The most common adverse reactions, reported in at least 2 CREON-treated patients (greater than or equal to 4%) and at a higher rate than in placebo-treated patients in Studies 1 and 2, are shown in Table 1.

Table 1: Adverse Reactions* in Clinical Trials of Adult and Pediatric Patients 7 Years of Age and Older with Exocrine Pancreatic Insufficiency due to Cystic Fibrosis (Studies 1 and 2)
Adverse Reaction | CREON N = 49 n (%) | Placebo N = 47 n (%)
Vomiting | 3 (6%) | 1 (2%)
Dizziness | 2 (4%) | 1 (2%)
Cough | 2 (4%) | 0 (0%)

* Reported in at least 2 CREON-treated patients (greater than or equal to 4%) and at a higher rate than placebo-treated patients.

In Study 1, one patient experienced duodenitis and gastritis of moderate severity 16 days after completing treatment with CREON. Transient neutropenia without clinical sequelae was observed as an abnormal laboratory finding in one patient receiving CREON and a macrolide antibiotic.

Pediatric Patients 4 Months to 6 Years of Age

Adverse reactions reported in 18 CREON-treated pediatric patients aged 4 months to 6 years in Study 3 were vomiting, irritability, and decreased appetite, each occurring in 6% of patients [see Use in Specific Populations (8.4)].

Exocrine Pancreatic Insufficiency Due to Chronic Pancreatitis or Pancreatectomy in Adults

Adverse reactions reported in at least 1 adult CREON-treated patient (greater than or equal to 4%) and at a higher rate than in placebo-treated patients in Study 4 is shown in Table 2.

Table 2: Adverse Reactions* in a Clinical Trial of Adult Patients with Exocrine Pancreatic Insufficiency Due to Chronic Pancreatitis or Pancreatectomy (Study 4)
Adverse Reaction | CREON N = 25 n (%) | Placebo N = 29 n (%)
Hyperglycemia | 2 (8%) | 2 (7%)
Hypoglycemia | 1 (4%) | 1 (3%)
Abdominal Pain | 1 (4%) | 1 (3%)
Abnormal Feces | 1 (4%) | 0 (0%)
Flatulence | 1 (4%) | 0 (0%)
Frequent Bowel Movements | 1 (4%) | 0 (0%)
Nasopharyngitis | 1 (4%) | 0 (0%)

* Reported in at least 1 CREON-treated patient (greater than or equal to 4%) and at a higher rate than placebo-treated patients.

6.2 Postmarketing Experience

The following adverse reactions have been identified during post-approval use of CREON or other pancreatic enzyme products. Because these reactions are reported voluntarily from a population of uncertain size, it is not always possible to reliably estimate their frequency or establish a causal relationship to drug exposure.

Eye Disorders

- blurred vision

Gastrointestinal Disorders

- fibrosing colonopathy and distal intestinal obstruction syndrome
- abdominal pain, diarrhea, flatulence, constipation, and nausea

Immune System Disorders

- anaphylaxis, asthma, hives, and pruritus

Investigations

- asymptomatic elevations of liver enzymes

Musculoskeletal System

- myalgia, muscle spasm

Skin and Subcutaneous Tissue Disorders

- urticaria and rash

8 USE IN SPECIFIC POPULATIONS

8.1 Pregnancy

Risk Summary

Published data from case reports with pancrelipase use in pregnant women have not identified a drug-associated risk of major birth defects, miscarriage or other adverse maternal or fetal outcomes. Pancrelipase is minimally absorbed systematically; therefore, maternal use is not expected to result in fetal exposure to the drug. Animal reproduction studies have not been conducted with pancrelipase.

The background risk of major birth defects and miscarriage for the indicated populations is unknown. All pregnancies have a background risk of birth defect, loss, or other adverse outcomes. In the U.S. general population, the estimated background risk of major birth defects and miscarriage in clinically recognized pregnancies is 2 to 4% and 15 to 20%, respectively.

8.2 Lactation

Risk Summary

There are no data on the presence of pancrelipase in either human or animal milk, the effects on the breastfed infant or the effects on milk production. Pancrelipase is minimally absorbed systemically following oral administration; therefore, maternal use is not expected to result in clinically relevant exposure of breastfed infants to the drug. The developmental and health benefits of breastfeeding should be considered along with the mother’s clinical need for CREON and any potential adverse effects on the breastfed infant from CREON or from the underlying maternal condition.

8.4 Pediatric Use

The safety and effectiveness of CREON for the treatment of exocrine pancreatic insufficiency have been established in pediatric patients.

Use of CREON for this indication is supported by two adequate and well-controlled trials in adult and pediatric patients 12 years and older (Study 1) and in pediatric patients 7 to 11 years of age (Study 2) along with supportive data from an open-label, single-arm, study in 18 pediatric patients 4 months to six years of age (Study 3). All three study populations consisted of patients with exocrine pancreatic insufficiency due to cystic fibrosis. The safety in pediatric patients 7 years of age and older in Studies 1 and 2 were similar to that observed adult patients [see Adverse Reactions (6.1) and Clinical Studies (14)].

In Study 3, patients received their usual pancreatic enzyme replacement therapy (mean dose of 7,000 lipase units/kg/day for a mean duration of 18.2 days) followed by CREON (mean dose of 7,500 lipase units/kg/day for a mean duration of 12.6 days). The mean daily fat intake was 48 grams during treatment with usual pancreatic enzyme replacement therapy and 47 grams during treatment with CREON. Adverse reactions that occurred in patients during treatment with CREON in Study 3 were vomiting, irritability, and decreased appetite [see Adverse Reactions (6.1)].

Dosages exceeding 6,000 lipase units/kg/meal have been reported postmarketing to be associated with fibrosing colonopathy and colonic strictures in pediatric patients less than 12 years of age. If there is a history of fibrosing colonopathy, monitor patients during treatment with CREON because some patients may be at risk of progressing to stricture formation. Do not exceed the recommended dosage of either 2,500 lipase units/kg/meal, 10,000 lipase units/kg/day, or 4,000 lipase units/g fat ingested/day in pediatric patients greater than 12 months of age without further investigation [see Dosage and Administration (2.2) and Warnings and Precautions (5.1)].

Crushing or chewing CREON capsules or mixing the capsule contents in foods having a pH greater than 4.5 can disrupt the protective enteric coating on the capsule contents and result in early release of enzymes, irritation of the oral mucosa, and/or loss of enzyme activity. Instruct the patient or caregiver of the following: consume sufficient liquids (juice, water, breast milk, or formula) to ensure complete swallowing, and visually inspect the mouth of pediatric patients less than 12 months of age to ensure no drug is retained in the mouth and irritation of the oral mucosa has not occurred [see Dosage and Administration (2.3) and Warnings and Precautions (5.2)].

8.5 Geriatric Use

Clinical studies of CREON did not include sufficient numbers of patients aged 65 years and over to determine whether they respond differently from younger patients. Other reported clinical experience has not identified differences in responses between patients aged 65 years and over and younger adult patients.

10 OVERDOSAGE

Chronic high dosages of pancreatic enzyme products have been associated with fibrosing colonopathy and colonic strictures [see Warnings and Precautions (5.1)]. High dosages of pancreatic enzyme products have been associated with hyperuricosuria and hyperuricemia [see Warnings and Precautions (5.3)].

11 DESCRIPTION

Pancrelipase is a pancreatic enzyme product consisting of a mixture of enzymes including lipases, proteases, and amylases and is an extract derived from porcine pancreatic glands. The enteric-coated spheres in CREON are formulated to release pancreatic enzymes at an approximate pH of 5.5 or greater.

CREON (pancrelipase) delayed-release capsules are for oral administration, include a two-piece shell containing tan-colored enteric-coated spheres (0.71 mm to 1.60 mm in diameter), and are available as follows:

3,000 USP units of lipase; 9,500 USP units of protease; and 15,000 USP units of amylase; delayed-release capsules with shells that contain hypromellose and titanium dioxide, and that also may contain carrageenan and potassium chloride.

6,000 USP units of lipase; 19,000 USP units of protease; and 30,000 USP units of amylase; delayed-release capsules with shells that may contain gelatin, hypromellose, carrageenan, potassium chloride, sodium lauryl sulfate, titanium dioxide, FD&C Blue No. 1, and FD&C Blue No. 2, red iron oxide, and yellow iron oxide.

12,000 USP units of lipase; 38,000 USP units of protease; and 60,000 USP units of amylase; delayed-release capsules with shells that may contain gelatin, hypromellose, carrageenan, potassium chloride, sodium lauryl sulfate, titanium dioxide, black iron oxide, red iron oxide, and yellow iron oxide.

24,000 USP units of lipase; 76,000 USP units of protease; and 120,000 USP units of amylase; delayed-release capsules with shells that may contain gelatin, hypromellose, carrageenan, potassium chloride, sodium lauryl sulfate, titanium dioxide, red iron oxide, and yellow iron oxide.

36,000 USP units of lipase; 114,000 USP units of protease; and 180,000 USP units of amylase; delayed-release capsules with shells that may contain gelatin, hypromellose, carrageenan, potassium chloride, sodium lauryl sulfate, titanium dioxide, FD&C Blue No. 1, and FD&C Blue No. 2.

CREON (pancrelipase) delayed-release capsules include the following inactive ingredients: cetyl alcohol, dimethicone, hypromellose phthalate, polyethylene glycol, and triethyl citrate.

12 CLINICAL PHARMACOLOGY

12.1 Mechanism of Action

Pancreatic enzyme products contain a mixture of lipases, proteases, and amylases that catalyze the hydrolysis of fats to monoglyceride, glycerol and free fatty acids, proteins into peptides and amino acids, and starches into dextrins and short chain sugars such as maltose and maltriose in the duodenum and proximal small intestine, thereby acting like digestive enzymes physiologically secreted by the pancreas.

12.2 Pharmacodynamics

For patients consuming a high fat diet in the clinical trials, the coefficient of fat absorption (CFA) was higher in patients who received CREON compared to the placebo treatment group, indicating improved fat absorption [see Clinical Studies (14.1,14.2)].

12.3 Pharmacokinetics

Following oral administration, the lipases, proteases, and amylases released from CREON are not absorbed from the gastrointestinal tract in appreciable amounts.

Drug Interactions

The lipases, proteases, and amylases of CREON are not substrates of CYP enzymes or transporters. CYP enzymes or transporters mediated drug interactions are not expected.

14 CLINICAL STUDIES

14.1 Exocrine Pancreatic Insufficiency Due to Cystic Fibrosis

Adult and Pediatric Patients

Studies 1 and 2 were randomized, double-blind, placebo-controlled, crossover studies in 49 patients, aged 7 to 43 years, with exocrine pancreatic insufficiency due to cystic fibrosis.

- Study 1 included patients aged 12 to 43 years (n = 32). The final analysis population was limited to 29 patients; 3 patients were excluded due to protocol deviations.
- Study 2 included patients aged 7 to 11 years (n = 17). The final analysis population was limited to 16 patients; 1 patient withdrew consent prior to stool collection during treatment with CREON.

In each study, patients were randomized to receive CREON at a dose of 4,000 lipase units/g fat ingested/day or matching placebo for 5 to 6 days of treatment, followed by crossover to the alternate treatment for an additional 5 to 6 days. All patients consumed a high-fat diet (greater than or equal to 90 grams of fat per day, 40% of daily calories derived from fat) during the treatment periods.

Coefficient of Fat Absorption Endpoint and Results

The primary efficacy endpoint was the coefficient of fat absorption (CFA) in CREON and placebo treatment groups. The coefficient of fat absorption (CFA) was determined by a 72-hour stool collection during both treatments, when both fat excretion and fat ingestion were measured. Each patient's CFA during placebo treatment was used as their no-treatment CFA value.

In Study 1, mean CFA was 89% with CREON treatment compared to 49% with placebo treatment. The mean difference in CFA was 41 percentage points in favor of CREON treatment with 95% CI: (34, 47) and p<0.001.

In Study 2, mean CFA was 83% with CREON treatment compared to 47% with placebo treatment. The mean difference in CFA was 35 percentage points in favor of CREON treatment with 95% CI: (27, 44) and p<0.001.

Subgroup analyses of the CFA results in Studies 1 and 2 showed that mean change in CFA with CREON treatment was greater in patients with lower no-treatment (placebo) CFA values than in patients with higher no-treatment (placebo) CFA values. There were no differences in response to CREON by age or biological sex, with similar responses to CREON observed in male and female patients, and in younger (under 18 years of age) and older patients.

Coefficient of Nitrogen Absorption Endpoint and Results

The coefficient of nitrogen absorption (CNA) was determined by a 72-hour stool collection during both treatments, when nitrogen excretion was measured and nitrogen ingestion from a controlled diet was estimated (based on the assumption that proteins contain 16% nitrogen). Each patient's CNA during placebo treatment was used as their no-treatment CNA value.

- In Study 1, mean CNA was 86% with CREON treatment compared to 49% with placebo treatment. The mean difference in CNA was 37 percentage points in favor of CREON treatment with 95% CI: (31, 42) and p<0.001.
- In Study 2, mean CNA was 80% with CREON treatment compared to 45% with placebo treatment. The mean difference in CNA was 35 percentage points in favor of CREON treatment with 95% CI: (26, 45) and p<0.001.

14.2 Exocrine Pancreatic Insufficiency Due to Chronic Pancreatitis or Pancreatectomy

A randomized, double-blind, placebo-controlled, parallel group study was conducted in 54 adult patients, aged 32 to 75 years, with exocrine pancreatic insufficiency due to chronic pancreatitis or pancreatectomy (Study 4). The final analysis population was limited to 52 patients; 2 patients were excluded due to protocol violations. Ten patients had a history of pancreatectomy (7 were treated with CREON). In this study, patients received placebo for 5 days (run-in period), followed by pancreatic enzyme replacement therapy as directed by the investigator for 16 days; this was followed by randomization to CREON or matching placebo for 7 days of treatment (double-blind period). Only patients with CFA less than 80% in the run-in period were randomized to the double-blind period. All patients were to consume a high-fat diet (greater than or equal to 100 grams of fat/day) during the treatment period. The dosage of CREON during the double-blind period was 72,000 lipase units per main meal (3 main meals) and 36,000 lipase units per snack (2 snacks) [approximately 1,000 lipase units/kg/meal]. The mean exposure to CREON during this study was 7 days in the 25 patients that received CREON.

Coefficient of Fat Absorption Endpoint and Results

The CFA was determined by a 72-hour stool collection during the run-in and double-blind treatment periods, when both fat excretion and fat ingestion were measured. The mean change in CFA from the run-in period to the end of the double-blind period in the CREON and placebo groups is shown in Table 3.

Table 3: Change in Coefficient of Fat Absorption in Adults with Exocrine Pancreatic Insufficiency Due to Chronic Pancreatitis and Pancreatectomy (Study 4)
 | CREON N = 24 | Placebo N = 28
CFA [%]
Run-in Period (Mean, SD) | 54 (19) | 57 (21)
End of Double-Blind Period (Mean, SD) | 86 (6) | 66 (20)
Change in CFA * [%]
Run-in Period to End of Double-Blind Period (Mean, SD) | 32 (18) | 9 (13)
Treatment Difference (95% CI) | 21 (14, 28)
*p<0.0001

Subgroup analyses of the CFA results showed that mean change in CFA was greater in patients with lower run-in period CFA values than in patients with higher run-in period CFA values. Only 1 of the patients with a history of total pancreatectomy was treated with CREON in the study. That patient had a CFA of 26% during the run-in period and a CFA of 73% at the end of the double-blind period. The remaining 6 patients with a history of partial pancreatectomy treated with CREON on the study had a mean CFA of 42% during the run-in period and a mean CFA of 84% at the end of the double-blind period.

16 HOW SUPPLIED/STORAGE AND HANDLING

CREON (pancrelipase) delayed-release capsules, containing tan-colored enteric-coated pancrelipase spheres, are supplied as follows:

Strength | Description | Supplied As | NDC Number
3,000 USP units of lipase; 9,500 USP units of protease; 15,000 USP units of amylase | Two-piece hypromellose capsule, white opaque cap imprinted “CREON 1203”, white opaque body | Bottles of 70 | 0032-0045-70
 |  |  | 0032-1203-70
6,000 USP units of lipase; 19,000 USP units of protease; 30,000 USP units of amylase | Two-piece hypromellose capsule, orange opaque cap imprinted “CREON 1206”, blue opaque body | Bottles of 100 | 0032-0046-70
 | Two-piece gelatin capsule, orange opaque cap imprinted “CREON 1206”, blue opaque body | Bottles of 100 | 0032-1206-01
 |  | Bottles of 250 | 0032-1206-07
12,000 USP units of lipase; 38,000 USP units of protease; 60,000 USP units of amylase | Two-piece hypromellose capsule, brown opaque cap imprinted “CREON 1212”, colorless transparent body | Bottles of 100 | 0032-0047-70
 | Two-piece gelatin capsule, brown opaque cap imprinted “CREON 1212”, colorless transparent body | Bottles of 100 | 0032-1212-01
 |  | Bottles of 250 | 0032-1212-07
24,000 USP units of lipase; 76,000 USP units of protease; 120,000 USP units of amylase | Two-piece hypromellose capsule, orange opaque cap imprinted “CREON 1224”, colorless transparent body | Bottles of 100 | 0032-2636-01
 |  | Bottles of 240 | 0032-2636-70
 | Two-piece gelatin capsule, orange opaque cap imprinted “CREON 1224”, colorless transparent body | Bottles of 100 | 0032-1224-01
 |  | Bottles of 250 | 0032-1224-07
36,000 USP units of lipase; 114,000 USP units of protease; 180,000 USP units of amylase | Two-piece hypromellose capsule, blue opaque cap imprinted “CREON 1236”, colorless transparent body | Bottles of 100 | 0032-2637-01
 |  | Bottles of 240 | 0032-2637-70
 | Two-piece gelatin capsule, blue opaque cap imprinted “CREON 1236”, colorless transparent body | Bottles of 100 | 0032-3016-13
 |  | Bottles of 250 | 0032-3016-28

Storage and Handling

- Store CREON at room temperature, 15°C to 25°C (59°F to 77°F), and protect from moisture. Temperature excursions are permitted between 25°C to 40°C (77°F to 104°F) for up to 30 days. Discard CREON if exposed to higher temperature and moisture conditions higher than 70%.
- After opening, keep bottle tightly closed between uses to protect from moisture. Keep the desiccant in the bottle if present.
- Store and dispense CREON in the original container.

17 PATIENT COUNSELING INFORMATION

Advise the patient or caregiver to read the FDA-approved patient labeling (Medication Guide).

Fibrosing Colonopathy

Advise the patient or caregiver that fibrosing colonopathy has been reported with high dosages of pancreatic enzyme products, usually with use over a prolonged period of time and in pediatric patients with cystic fibrosis. Colonic stricture has been reported in pediatric patients less than 12 years of age. Advise patients and caregivers that if signs and symptoms of colon stricture formation occur (e.g., stomach area (abdominal) pain, bloating, trouble passing stool (constipation), nausea, vomiting, diarrhea) to immediately contact their healthcare provider [see Warnings and Precautions (5.1)].

Hyperuricemia

Advise the patient or caregiver that hyperuricemia may occur in patients with gout or renal impairment and to contact the healthcare provider if they experience pain, stiffness, redness or swelling of their joints [see Warnings and Precautions (5.3)].

Hypersensitivity Reactions

Inform the patient or caregiver that severe hypersensitivity reactions, including anaphylaxis, asthma, hives, and pruritus, have been reported with use of pancreatic enzyme products. Seek medical attention if signs or symptoms of a hypersensitivity reaction develop [see Warnings and Precautions (5.5)].

Dosage

Advise the patient or caregiver to take or administer CREON as prescribed, and to contact the healthcare provider if signs and symptoms of malabsorption persist [see Dosage and Administration (2.2)].

Administration

Instruct the patient or caregiver as follows:

- Take CREON during meals and snacks.
- Swallow capsules whole.
- For adult and pediatric patients unable to swallow intact capsules, the capsule contents may be sprinkled on a small amount of soft acidic food with a pH of 4.5 or less (e.g., applesauce, bananas, plain Greek yogurt). For pediatric patients birth to 12 months of age, CREON capsules can also be opened, and the capsule contents sprinkled directly into the infant’s mouth.
- Consume sufficient liquids (juice, water, breast milk, or formula) and visually inspect an infant’s mouth to ensure complete swallowing of CREON capsules or capsule contents [see Warnings and Precautions (5.2)].
- Do not crush or chew CREON capsules or capsule contents.
- Do not mix the CREON capsule contents directly into a bottle of breast milk or formula.

Storage

Instruct the patient or caregiver as follows:

- Keep CREON in a dry place and protect from heat.
- After opening, keep the bottle tightly closed between uses to protect from moisture.
- Keep CREON in the original container.
- If there is a desiccant packet in the bottle, keep it in the bottle. Do not eat or throw away the desiccant.

© 2009-2024 AbbVie. All rights reserved.

CREON® is a registered trademark of AbbVie Products LLC.

Manufactured by:

AbbVie Inc.

North Chicago, IL 60064, U.S.A.

US License Number 1889

20082735 February, 2024

MEDICATION GUIDE
CREON® (krē ′ŏn)
(pancrelipase)
delayed-release capsules, for oral use

What is the most important information I should know about CREON?
CREON may increase your chance of having a rare bowel disorder called fibrosing colonopathy especially if taken at a high dose for a long time in children with cystic fibrosis. This condition is serious and may require surgery. The risk of having this condition may be reduced by following the dosing instructions that your healthcare provider gave you. Call your healthcare provider right away if you have any unusual or severe:

- stomach area (abdominal) pain
- bloating
- trouble passing stool (having bowel movements)
- nausea, vomiting, or diarrhea

Take CREON exactly as prescribed. Do not take more or less CREON than directed by your healthcare provider.

What is CREON?
CREON is a prescription medicine used to treat people who cannot digest food normally because their pancreas does not make enough enzymes.
CREON contains a mixture of digestive enzymes including lipases, proteases, and amylases from pig pancreas.
CREON is safe and effective in adults and children.

Before you take CREON, tell your healthcare provider about all your medical conditions, including if you:

- are allergic to pork (pig) products.
- have a history of blockage of your intestines, or scarring or thickening of your bowel wall (fibrosing colonopathy).
- have gout, kidney disease, or high blood uric acid (hyperuricemia).
- have trouble swallowing capsules.
- have any other medical condition.
- are pregnant or plan to become pregnant.
- are breastfeeding or plan to breastfeed. It is not known if CREON passes into your breast milk. Talk to your healthcare provider about the best way to feed your baby if you take CREON.

Tell your healthcare provider about all the medicines you take, including prescription and over-the-counter medicines, vitamins, and herbal supplements.
Know the medicines you take. Keep a list of them and show it to your healthcare provider and pharmacist when you get a new medicine.

How should I take CREON?

- Take CREON exactly as your healthcare provider tells you. Contact your healthcare provider if you continue to have signs and symptoms of malabsorption (not absorbing nutrients from food) such as abdominal pain, abdominal distention, bloating, fatty stools, or weight loss. Your dose may need to be changed.
- You should not switch CREON with any other pancreatic enzyme product without first talking to your healthcare provider.
- Do not take more capsules in a day than the number your healthcare provider tells you to take (total daily dose).
- Always take CREON with a meal or snack and enough liquid (water, juice, breast milk, or formula) to swallow CREON completely. If you eat a lot of meals or snacks in a day, be careful not to go over your total daily dose.
- Your healthcare provider may change your dose based on the amount of fatty foods you eat or based on your weight.
- CREON capsules should be swallowed whole. Do not crush or chew CREON capsules or its contents, and do not hold the capsule or capsule contents in your mouth. Crushing, chewing or holding the CREON capsules in your mouth may cause irritation in your mouth or change the way CREON works in your body.

Giving CREON to Adults and Children Older than 12 Months of Age

- Swallow CREON capsules whole without crushing or chewing them.
- If you have trouble swallowing capsules:
  - Carefully open the capsules and sprinkle the entire contents on small amounts of acidic soft food such as applesauce, bananas, or plain Greek yogurt. Ask your healthcare provider about other foods you can use.
  - Mix the capsule contents with the soft food. Do not crush the contents.
  - Swallow the mixture right away. Do not save it for later use.
- Drink enough water or juice right away to make sure the medicine is swallowed completely.
- If you forget to take CREON, call your healthcare provider or wait until your next meal and take your usual number of capsules. Take your next dose at your usual time. Do not make up for missed doses.

Giving CREON to Infants (Children from Birth up to 12 Months of Age)

- Give CREON right before each breastfeeding or feeding formula.
- Do not mix CREON capsule contents directly into formula or breast milk.
- Carefully open the capsule and do one of the following:
  - Sprinkle the entire contents directly into your child’s mouth or
  - Mix the entire contents in a small amount of acidic soft food such as applesauce, bananas, or plain Greek yogurt as described in the previous section. These foods should be the kind found in baby food jars that you buy at the store, or other food recommended by your healthcare provider. Give the mixture to your child right away. Do not save it for later use.
- Give your child additional breast milk or formula right after CREON to completely swallow the medicine. Look in your child's mouth to make sure that it was all swallowed.
- If a dose is missed give the next dose with the next feeding.

What are the possible side effects of CREON?
CREON may cause serious side effects, including:

- See “What is the most important information I should know about CREON?”
- Irritation of the inside of your mouth. This can happen if CREON is not swallowed completely.
- Increase in blood uric acid levels (hyperuricemia). This may happen in people with gout, kidney problems, or those who take high doses of pancrelipase, the active ingredient in CREON. Call your healthcare provider if you have pain, stiffness, redness or swelling of your joints.
- Severe allergic reactions. Severe allergic reactions have happened in people taking pancreatic enzyme products like CREON. Stop taking CREON and get emergency treatment right away if you have any of these symptoms: trouble with breathing, skin rashes, swollen lips, or itching.

The most common side effects of CREON include:

- Blood sugar increase (hyperglycemia) or decrease (hypoglycemia)
- Pain in your stomach (abdominal area)
- Frequent or abnormal bowel movements
- Gas
- Vomiting
- Dizziness
- Sore throat and cough

Other Possible Side Effects:
CREON and other pancreatic enzyme products are made from the pancreas of pigs, the same pigs people eat as pork. These pigs may carry viruses. Although it has never been reported, it may be possible for a person to get a viral infection from taking pancreatic enzyme products that come from pigs.
Tell your healthcare provider if you have any side effect that bothers you or that does not go away.
These are not all the possible side effects of CREON. Call your doctor for medical advice about side effects. You may report side effects to FDA at 1-800-FDA-1088.
You may also report side effects to AbbVie Inc. at 1-800-633-9110.

How should I store CREON?

- Store CREON at room temperature between 59°F to 77°F (15°C to 25°C). Avoid heat.
- You may store CREON at a temperature between 77°F to 104°F (25°C to 40°C) for up to 30 days. Throw away any CREON stored at these temperatures for more than 30 days.
- Keep CREON in a dry place and in the original container.
- After opening the bottle, keep it closed tightly between uses to protect from moisture. If there is a moisture-absorbing packet (desiccant) in the bottle, keep it in the bottle. Do not eat it or throw it away.

Keep CREON and all medicines out of the reach of children.

General information about the safe and effective use of CREON.
Medicines are sometimes prescribed for purposes other than those listed in a Medication Guide. Do not use CREON for a condition for which it was not prescribed. Do not give CREON to other people to take, even if they have the same symptoms you have. It may harm them.
You can ask your healthcare provider or pharmacist for information about CREON that is written for healthcare professionals.

What are the ingredients in CREON?
Active Ingredient: lipase, protease, amylase
Inactive Ingredients: cetyl alcohol, dimethicone, hypromellose phthalate, polyethylene glycol, and triethyl citrate.
The shells for the CREON 3,000 USP units of lipase strength capsules contain hypromellose and titanium dioxide. They also may contain carrageenan and potassium chloride.
The shells of the CREON 6,000 USP units of lipase strength capsules may contain gelatin, hypromellose, carrageenan, potassium chloride, sodium lauryl sulfate, titanium dioxide, FD&C Blue No. 1, FD&C Blue No. 2, red iron oxide, and yellow iron oxide.
The shells of the CREON 12,000 USP units of lipase strength capsules may contain gelatin, hypromellose, carrageenan, potassium chloride, sodium lauryl sulfate, titanium dioxide, black iron oxide, red iron oxide, and yellow iron oxide.
The shells for the CREON 24,000 USP units of lipase strength capsules may contain gelatin, hypromellose, carrageenan, potassium chloride, sodium lauryl sulfate, titanium dioxide, red iron oxide, and yellow iron oxide.
The shells of the CREON 36,000 USP units of lipase strength capsules may contain gelatin, hypromellose, carrageenan, potassium chloride, sodium lauryl sulfate, titanium dioxide, FD&C Blue No. 1, and FD&C Blue No. 2.
Manufactured by:
AbbVie Inc.
North Chicago, IL 60064, U.S.A.
US License Number 1889
© 2009-2024 AbbVie Inc.
For more information, go to www.creon-us.com or call toll-free (1-800-633-9110).

This Medication Guide has been approved by the U.S. Food and Drug Administration. Revised: 2/2024

20082735

PACKAGE LABEL

NDC 0032-0045-70
70 Delayed-Release Capsules
Rx only
pancrelipase
CREON®
Delayed-Release Capsules
DOSE BY LIPASE UNITS
Lipase 3,000 USP Units
Protease 9,500 USP Units
Amylase 15,000 USP Units
Each delayed-release capsule contains
pancrelipase in enteric-coated spheres.
Dispense enclosed Medication Guide to each patient.

PACKAGE LABEL

NDC 0032-0046-70
100 Delayed-Release Capsules
Rx only
pancrelipase
CREON®
Delayed-Release Capsules
DOSE BY LIPASE UNITS
Lipase 6,000 USP Units
Protease 19,000 USP Units
Amylase 30,000 USP Units
Each delayed-release capsule contains
pancrelipase in enteric-coated spheres.
Dispense enclosed Medication Guide to each patient.

PACKAGE LABEL

NDC 0032-0047-70
100 Delayed-Release Capsules
Rx only
pancrelipase
CREON®
Delayed-Release Capsules
DOSE BY LIPASE UNITS
Lipase 12,000 USP Units
Protease 38,000 USP Units
Amylase 60,000 USP Units
Each delayed-release capsule contains
pancrelipase in enteric-coated spheres.
Dispense enclosed Medication Guide to each patient.

PACKAGE LABEL

NDC 0032-1203-70
70 Delayed-Release Capsules
Pancrelipase
CREON®
Delayed-Release Capsules
DOSE BY LIPASE UNITS
Lipase 3,000 USP Units
Protease 9,500 USP Units
Amylase 15,000 USP Units
Each delayed-release capsule
contains pancrelipase in
enteric-coated spheres.
Dispense enclosed Medication
Guide to each patient.
Rx only
abbvie

PACKAGE LABEL

NDC 0032-1206-01
100 Delayed-Release Capsules
pancrelipase
CREON®
Delayed-Release Capsules
DOSE BY LIPASE UNITS
Lipase 6,000 USP Units
Protease 19,000 USP Units
Amylase 30,000 USP Units
Each delayed-release capsule contains
pancrelipase in enteric-coated spheres.
Dispense enclosed Medication
Guide to each patient.
Rx only
abbvie

PACKAGE LABEL

NDC 0032-1212-07
250 Delayed-Release Capsules
pancrelipase
CREON®
Delayed-Release Capsules
DOSE BY LIPASE UNITS
Lipase 12,000 USP Units
Protease 38,000 USP Units
Amylase 60,000 USP Units
Each delayed-release capsule
contains pancrelipase in
enteric-coated spheres.
Dispense enclosed
Medication Guide
to each patient.
Rx only
abbvie

PACKAGE LABEL

NDC 0032-1224-01
100 Delayed-Release Capsules
pancrelipase
CREON®
Delayed-Release Capsules
DOSE BY LIPASE UNITS
Lipase 24,000 USP Units
Protease 76,000 USP Units
Amylase 120,000 USP Units
Each delayed-release capsule
contains pancrelipase in
enteric-coated spheres.
Dispense enclosed
Medication Guide
to each patient.
Rx only
abbvie

PACKAGE LABEL

NDC 0032-2636-70
240 Delayed-Release Capsules
pancrelipase
CREON®
Delayed-Release Capsules
DOSE BY LIPASE UNITS
Lipase 24,000 USP Units
Protease 76,000 USP Units
Amylase 120,000 USP Units
Each delayed-release capsule contains
pancrelipase in enteric-coated spheres.
Dispense enclosed Medication Guide to each patient.
Rx only
abbvie

PACKAGE LABEL

NDC 0032-2637-70
240 Delayed-Release Capsules
pancrelipase
CREON®
Delayed-Release Capsules
DOSE BY LIPASE UNITS
Lipase 36,000 USP Units
Protease 114,000 USP Units
Amylase 180,000 USP Unites
Each delayed-release capsule contains
pancrelipase in enteric-coated spheres.
Dispense enclosed Medication
Guide to each patient.
Rx only
abbvie

PACKAGE LABEL

NDC 0032-3016-13
100 Delayed-Release Capsules
pancrelipase
CREON®
Delayed-Release Capsules
DOSE BY LIPASE UNITS
Lipase 36,000 USP Units
Protease 114,000 USP Units
Amylase 180,000 USP Units
Each delayed-release capsule
contains pancrelipase in
enteric-coated spheres.
Dispense enclosed
Medication Guide
to each patient.
Rx only
abbvie